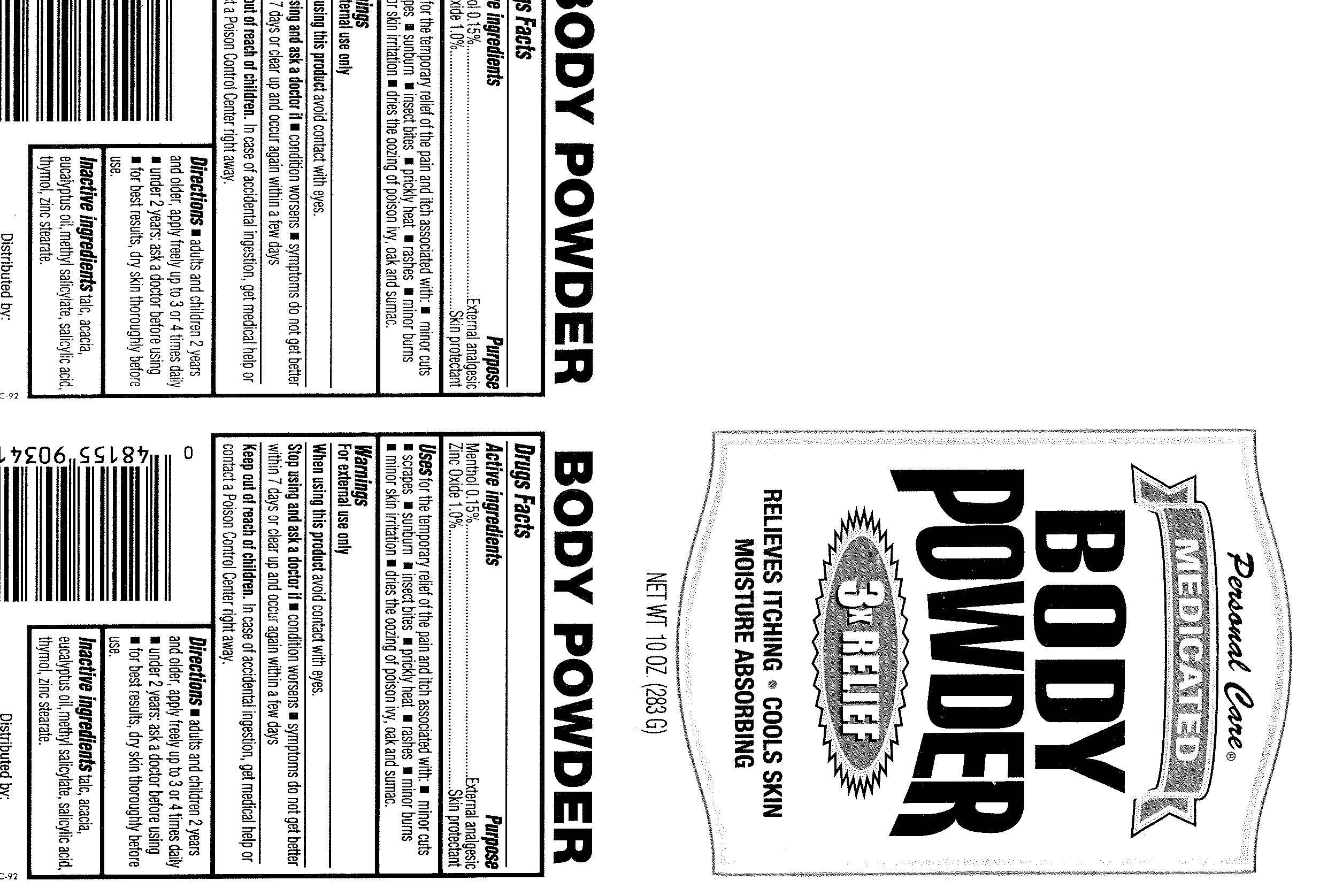 DRUG LABEL: Personal Care
NDC: 29500-9090 | Form: POWDER
Manufacturer: Personal Care Products, Inc.
Category: otc | Type: HUMAN OTC DRUG LABEL
Date: 20090907

ACTIVE INGREDIENTS: Menthol 3 mg/2 g; Zinc Oxide 20 mg/2 g
INACTIVE INGREDIENTS: Talc; Acacia; Eucalyptol; Methyl Salicylate; Salicylic Acid; Thymol; Zinc Stearate

Personal Care Medicated Body Powder

Active ingredients Purpose
Menthol 0.15 percent External analgesic
Zinc Oxide 1.0 percent Skin protectant

PURPOSE

Uses for the temporary relief of the pain and itch associated with:
- minor cuts - scrapes - sunburn - insect bites - prickly heat - rashes
- minor burns - minor skin irritation - dries the oozing of poison ivy, oak
and sumac.

Warnings
For external use only
When using this product avoid contact with eyes.

Stop using and ask a doctor if
- condition worsens
- symptoms do not get better within 7 days or clear up and occur again within a few days

Keep out of reach of children. In case of accidental ingestion, get medical help or
contact a Poison Control Center right away.

Directions
adults and children 2 years and older, apply freely up to 3 or 4 times daily
- under 2 years: ask a doctor before using
- for best results, dry skin thoroughly before use.

Inactive ingredients
talc, acacia, eucalyptus oil, methyl salicylate, salicylic acid, thymol, zinc stearate